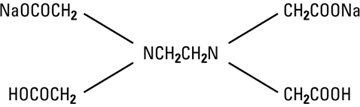 DRUG LABEL: Unknown
Category: prescription | Type: Human prescription drug label
Date: 20060511

ENDRATE®
EDETATE DISODIUM INJECTION, USP

FOR INTRAVENOUS INFUSION

ONLY AFTER DILUTION

Rx only

Ampul

WARNING

The use of this drug in any particular patient is recommended only when the severity of the clinical condition justifies the aggressive measures associated with this type of therapy.

DESCRIPTION

Endrate (Edetate Disodium Injection, USP) is a sterile, nonpyrogenic, concentrated solution of edetate disodium in water for injection which as a result of a pH adjustment with sodium hydroxide contains varying amounts of disodium and trisodium salts. After dilution, it is administered by intravenous infusion.

Each mL contains edetate disodium, anhydrous 150 mg. May contain sodium hydroxide for pH adjustment. pH is 7.0 (6.5 to 7.5).

Edetate disodium is classified as a clinical chelating agent for emergency lowering of serum calcium in hypercalcemia.

The solution contains no bacteriostat, antimicrobial agent or buffer (except for pH adjustment) and is intended only for use (after dilution) as a single-dose infusion. When smaller doses are required, the unused portion should be discarded.

Edetate Disodium, USP is chemically designated disodium (ethylenedinitrilo) tetraacetate dihydrate, a white crystalline powder soluble in water. It is also described as the disodium salt of ethylenediamine tetraacetic acid (EDTA) and has the following structural formula:

CLINICAL PHARMACOLOGY

Edetate Disodium Injection, USP forms chelates with the cations of calcium and many divalent and trivalent metals. Because of its affinity for calcium, edetate disodium will produce a lowering of the serum calcium level during intravenous infusion. Slow infusion over a protracted period may cause mobilization of extracirculatory calcium stores. Edetate disodiumexerts a negative inotropic effect upon the heart.

After intravenous administration, the chelate formed is excreted in the urine with 50% appearing in 1 hour and over 95% in 24 hours.

Edetate disodium likewise forms chelates with other polyvalent metals and produces increases in urinary excretion of magnesium, zinc and other trace elements. It does not form a chelate with potassium but may reduce the serum level and increase urinary loss of potassium.

INDICATIONS AND USAGE

Endrate (Edetate Disodium Injection, USP) is indicated in selected patients for the emergency treatment of hypercalcemia and for the control of ventricular arrhythmias associated with digitalis toxicity.

CONTRAINDICATIONS

Endrate (Edetate Disodium Injection, USP) is contraindicated in anuric patients. It is not indicated for the treatment of generalized arteriosclerosis associated with advancing age.

WARNINGS

See warning statement, page 1.

Rapid intravenous infusion or attainment of high serum concentration of edetate disodium may cause a precipitous drop in the serum calcium level and many result in fatality. Toxicity appears to be dependent upon both total dosage and speed of administration. The rate of administration and dosage should not exceed that indicated in DOSAGE AND ADMINISTRATION.

Because of its irritant effect on the tissues and because of the danger of serious side effects if administered in the undiluted form, Endrate (Edetate Disodium Injection, USP) should be diluted before infusion. See DOSAGE AND ADMINISTRATION.

PRECAUTIONS

After the infusion of edetate disodium, the patient should remain in bed for a short time because of the possibility of postural hypotension.

The possibility of an adverse effect on myocardial contractility should be considered when administering the drug to patients with heart disease. Caution is dictated in the use of this drug in patients with limited cardiac reserve or incipient congestive failure.

Edetate Disodium Injection, USP therapy should be used with caution in patients with clinical or subclinical potassium deficiency states. In such cases it is advisable to perform serum potassium blood levels for possible hypokalemia and to monitor ECG changes.

The possibility of hypomagnesemia should be kept in mind during prolonged therapy.

Treatment with edetate disodium has been shown to cause a lowering of blood sugar and insulin requirements in patients with diabetes who are treated with insulin.

Do not use unless solution is clear and container is intact. Discard unused portion.

Laboratory Test

Renal excretory function should be assessed prior to treatment. Periodic BUN and creatinine determinations and daily urinalysis should be performed on patients receiving this drug.

Because of the possibility of inducing an electrolyte imbalance during treatment with edetate disodium, appropriate laboratory determinations and studies to evaluate the status of cardiac function should be performed. Repetition of these tests is recommended as often as clinically indicated, particularly in patients with ventricular arrhythmia and those with a history of seizure disorders or intracranial lesions. If clinical evidence suggests any disturbance of liver function during treatment, appropriate laboratory determinations should be performed and withdrawal of the drug may be required.

Drug/Laboratory Test Interactions

The oxalate method of determining serum calcium tends to give low readings in the presence of edetate disodium; modification of this method, as by acidifying the sample or use of a different method may be required for accuracy. The least interference will be noted immediately before a subsequent dose is administered.

Carcinogenesis, Mutagenesis, Impairment of Fertility:

Definitive statements cannot be made due to insufficient data and conflicting information.

Pregnancy Category C.

Animal reproduction studies have not been conducted with Edetate Disodium Injection. It is also not known whether Edetate Disodium Injection can cause fetal harm when administered to a pregnant woman or can affect reproduction capacity. Edetate Disodium Injection should be given to a pregnant woman only if clearly needed.

Nursing Mothers:

The safety of this product in nursing mothers has not been established.

Pediatric Use:

Safety and effectiveness in pediatric patients have not been established.

Geriatric Use:

Clinical studies of Endrate® did not include sufficient numbers of patients aged 65 and over to determine whether they respond differently from younger subjects. Other reported clinical experience has not identified differences in responses between elderly and younger patients. In general, dose selection for an elderly patient should be cautious, reflecting the greater frequency of decreased hepatic, renal, or cardiac function, and of concomitant disease or other drug therapy.

This drug is known to be substantially excreted by the kidney, and the risk of toxic reactions to this drug may be greater in patients with impaired renal function. Because elderly patients are more likely to have decreased renal function, care should be taken in dose selection, and it may be useful to monitor renal function.

ADVERSE REACTIONS

Gastrointestinal symptoms such as nausea, vomiting and diarrhea are fairly common following administration of this drug. Transient symptoms such as circumoral paresthesia, numbness and headache and a transient drop in systolic and diastolic blood pressure may occur. Thrombophlebitis, febrile reactions, hyperuricemia, anemia, exfoliative dermatitis and other toxic skin and mucous membrane reactions have been reported.

Nephrotoxicity and damage to the reticuloendothelial system with hemorrhagic tendencies have been reported with excessive dosages.

OVERDOSAGE

Because of the possibility that Edetate Disodium Injection, USP may produce a precipitous drop in the serum calcium level, a source of calcium replacement suitable for intravenous administration (such as calcium gluconate) should be instantly available at the bedside before edetate disodium is administered. Extreme caution is dictated in the use of intravenous calcium in the treatment of tetany, especially in digitalized patients because the action of the drug and the replacement of calcium ions may produce a reversal of the desired digitalis effect.

DOSAGE AND ADMINISTRATION

Edetate Disodium Injection, USP is administered by intravenous infusion only after dilution.

For Adults: The recommended daily dosage is 50 mg/kg of body weight to a maximum dose of 3 g in 24 hours. The dose, calculated by body weight, should be diluted in 500 mL of 5% Dextrose Injection, USP or 0.9% Sodium Chloride Injection, USP. The intravenous infusion should be regulated so that three or more hours are required for completion and the cardiac reserve of the patient is not exceeded. A suggested regimen includes five consecutive daily doses followed by two days without medication, with repeated courses as necessary to a total of 15 doses.

Parenteral drug products should be inspected visually for particulate matter and discoloration prior to administration, whenever solution and container permit. See PRECAUTIONS.

Drug Interactions

Additives may be incompatible with the reconstituted (diluted) solution required for intravenous infusion. Consult with pharmacist, if available. When introducing additives, use aseptic technique, mix thoroughly and do not store.

HOW SUPPLIED

Endrate (Edetate Disodium Injection, USP) is supplied in 20 mL (3 g) ampuls, List No. 6940.

Store at 25°C (77°F) with excursions permitted between 15° to 30°C (59° to 86°F).

Rev: May, 2004

©Hospira 2004 | EN-0183 | Printed in USA

HOSPIRA, INC., LAKE FOREST, IL 60045 USA